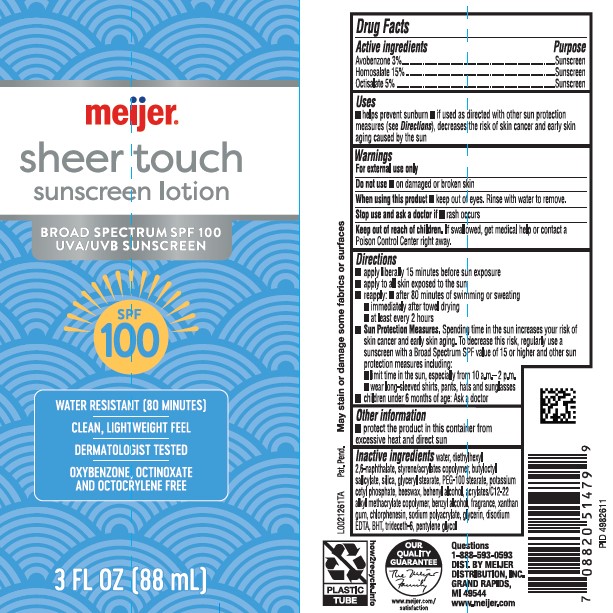 DRUG LABEL: Avobenzone, Homosalate, Octisalate
NDC: 79481-0934 | Form: LOTION
Manufacturer: Meijer, Inc.
Category: otc | Type: HUMAN OTC DRUG LABEL
Date: 20260224

ACTIVE INGREDIENTS: AVOBENZONE 30 mg/1 mL; HOMOSALATE 150 mg/1 mL; OCTISALATE 50 mg/1 mL
INACTIVE INGREDIENTS: WATER; DIETHYLHEXYL 2,6-NAPHTHALATE; BUTYL ACRYLATE/METHYL METHACRYLATE/METHACRYLIC ACID COPOLYMER (18000 MW); BUTYLOCTYL SALICYLATE; SILICON DIOXIDE; GLYCERYL MONOSTEARATE; PEG-100 STEARATE; POTASSIUM CETYL PHOSPHATE; YELLOW WAX; DOCOSANOL; BUTYL ACRYLATE/C16-C20 ALKYL METHACRYLATE/METHACRYLIC ACID/METHYL METHACRYLATE COPOLYMER; BENZYL ALCOHOL; XANTHAN GUM; CHLORPHENESIN; SODIUM POLYACRYLATE (8000 MW); GLYCERIN; EDETATE DISODIUM ANHYDROUS; BUTYLATED HYDROXYTOLUENE; TRIDECETH-6; PENTYLENE GLYCOL

Meijer D34.000/D34AA
Sheer Touch Sunscreen SPF 100

Active Ingredients

Avobenzone 3%

Homosalate 15%

Octisalate 5%

Purpose

Sunscreen

Uses

- helps prevent sunburn
- if used as directed with other sun protection measures (See Directions), decreases the risk of skin cancer and early skin aging caused by the sun

Warnings

For external use only

Do not use

- on damaged or broken skin

When using this product

- keep out of eyes. Rinse with water to remove.

Stop use and ask a doctor if

- rash occurs

Keep out of reach of children.

If swallowed, get medical help or contact a Poison Control right away.

Directions

- apply liberaly 15 minutes before sun exposure
- apply to all skin exposed to the sun
- reapply:
- after 80 minutes of swimming or sweating
- immediately after towel drying
- at least every 2 hours
- Sun Protection Measures. Spending time in the sun increases your risk of skin cancer and early skin aging. To decrease this risk, regularly use a sunscreen with Broad Spectrum SPF value of 15 or higher and other sun protection measures including:
- limit time in the sun, especialy from 10 a.m.-2 p.m.
- wear long-sleeved shirts, pants, hats and sunglasses
- children under 6 months of age: Ask a doctor

Other information

- protect the product in this container from excessive heat and direct sun

Inactive ingredients

water, diethylhexyl 2,6-naphthalate, styrene/acrylates copolymer, butyloctyl salicylate, silica, glyceryl stearate, PEG-100 stearate, potassium cetyl phosphate, beeswax, behenyl alcohol, acrylates/C12-22 alkyl methacrylate copolymer, benzyl alcohol, fragrance, xanthan gum, chlorphenesin, sodium polyacrylate, glycerin, disodium EDTA, BHT, trideceth-6, pentylene glycol

Disclaimer

May stain or damage some fabrics or surfaces.

Adverse Reaction

Questions

1-888-593-0593

DIST. BY MEIJER DISTRIBUTION INC.

GRAND RAPIDS, MI 49544

www.meijer.com

OUR QUALITY GUARANTEE

www.meijer.com/satisfaction

PLASTIC TUBE

how2recycle.info

Principal display panel

meijer®

sheer touch

sunscreen lotion

BROAD SPECTRUM SPF 100

UVA/UVB SUNSCREEN

SPF 100

WATER RESISTANT (80 MINUTES)

CLEAN, LIGHTWEIGHT FEEL

DERMATOLOGIST TESTED

OXYBENZONE, OXTINOXATE AND OCTOCRYLENE FREE

3 FL OZ (88 mL)